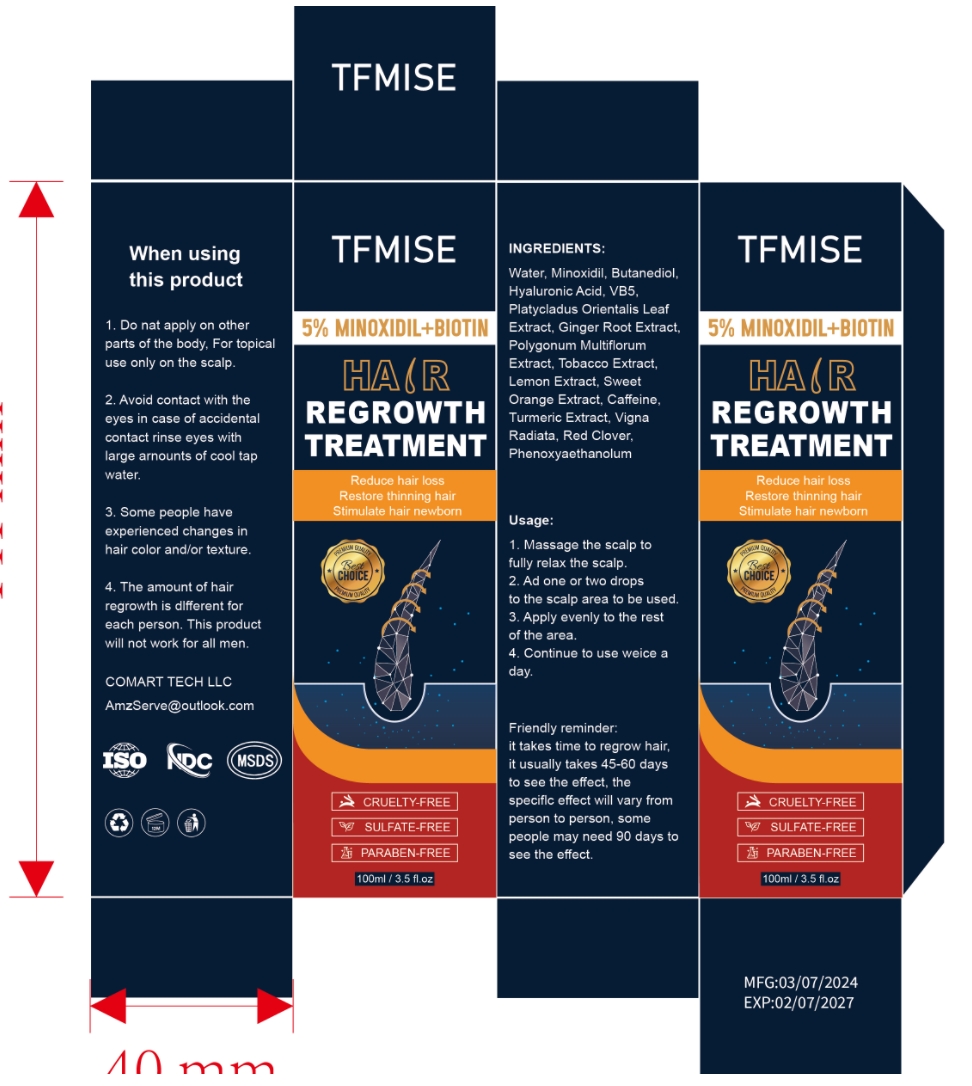 DRUG LABEL: TFMISE  HAIR REGROWTH TREATMENT
NDC: 84542-713 | Form: LIQUID
Manufacturer: COMART TECH LLC
Category: otc | Type: HUMAN OTC DRUG LABEL
Date: 20240722

ACTIVE INGREDIENTS: BIOTIN 5 g/100 mL
INACTIVE INGREDIENTS: MINOXIDIL; WATER; HYALURONIC ACID; RED CLOVER; PHENOXYETHANOL; CAFFEINE; PANTHENOL

ACTIVE INGREDIENT

Biotin：5%

PURPOSE

Hair Regrowth

INDICATIONS AND USAGE

1. Massage the scalp to fully relax the scalp.

2. Ad one or two drops to the scalp area to be used.

3. Apply evenly to the rest of the area.

4. Continue to use weice a day.

WARNINGS

For external use only.For external use only
Keep away from fire and flame

KEEP OUT OF REACH OF CHILDREN

If swallowed, get medical help or contact a Poison Control Center right away.

WHEN USING

1. Do not apply on other parts of the body, For topical use only on the scalp.

2. Avoid contact with the eyes in case of accidental contact rinse eyes with large arnounts of cool tap water.

3. Some people have experienced changes in hair color and/or texture.

4. The amount of hair regrowth is dlfferent for each person. This product will not work for all men.

Usage:1. Massage the scalp to fully relax the scalp.2. Ad one or two dropsto the scalp area to be used.3. Apply evenly to the rest of the area.4. Continue to use weice a day.

Friendly reminder: it takes time to regrow hair, it usually takes 45-60 days to see the effect, the speciflc effect will vary from person to person, some people may need 90 days to see the effect.

DO NOT USE

You have no family history of hair loss,hair loss is sudden and/or patchy.
You do not know the reason for you hair loss.
You ae under 18 years of age, Do not use it on babies and children your scalp is red,inflamed,infected, irritated, or painful.
You use other medicines on the scalp.Ask a doctor before use if you hace heart disease.

STOP USE

Chest pain, rapid heart beat, faintness, or dizziness occurs sudden, unexplained weight gain occurs,your hands or feet swell.

INACTIVE INGREDIENT

MINOXIDIL 5%

DOSAGE AND ADMINISTRATION

Twice each day, 4 sprays (1ml)each time. 50 days supply

TFMISE %5 BIOTIN AND MINOXIDIL HAIR REGROWTH TREATMENT

NGREDIENTS:Water,biotin, Minoxidil, Butanediol, Hyaluronic Acid, VB5, Platycladus Orientalis Leaf Extract, Ginger Root Extract,Polygonum MultiflorumExtract, Tobacco Extract, Lemon Extract, Sweet Orange Extract, Caffeine, Turmeric Extract, Vigna Radiata, Red Clover,Phenoxyaethanolum

When using this product

1. Do nat apply on other parts of the body, For topical use only on the scalp.

2. Avoid contact with the eyes in case of accidental contact rinse eyes with large arnounts of cool tap water.

3. Some people have experienced changes in hair color and/or texture.

4. The amount of hair regrowth is dlfferent for each person. This product will not work for all men.

Usage:1. Massage the scalp to fully relax the scalp.2. Ad one or two dropsto the scalp area to be used.3. Apply evenly to the rest of the area.4. Continue to use weice a day.

Friendly reminder: it takes time to regrow hair, it usually takes 45-60 days to see the effect, the speciflc effect will vary from person to person, some people may need 90 days to see the effect.